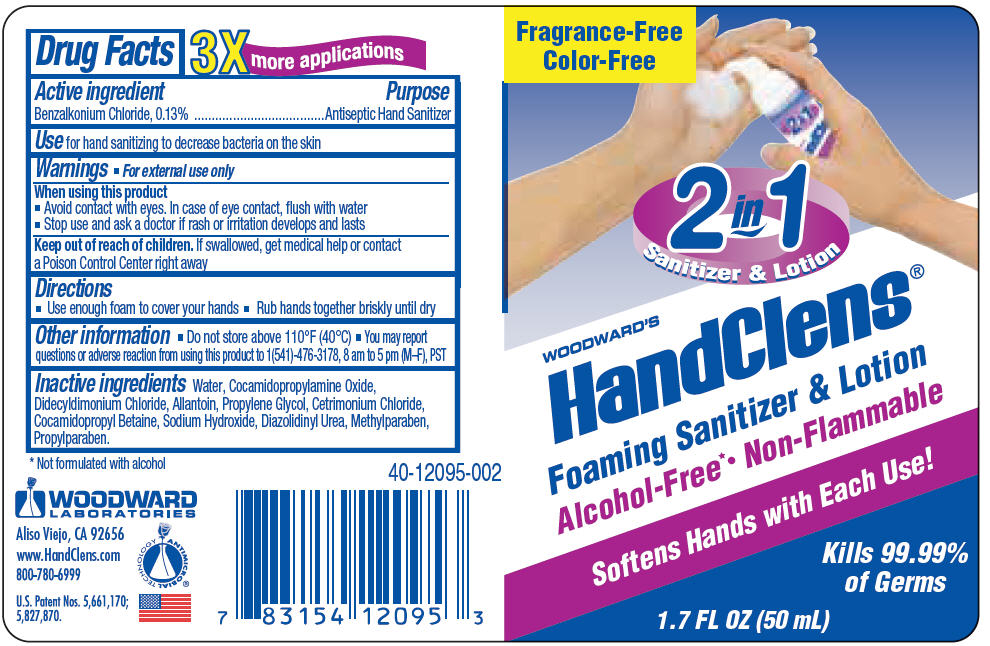 DRUG LABEL: WOODWARDS HANDCLENS FOAMING SANITIZER COLOR AND FRAGRANCE FREE
NDC: 60193-203 | Form: LIQUID
Manufacturer: Pacific World Corporation
Category: otc | Type: HUMAN OTC DRUG LABEL
Date: 20141020

ACTIVE INGREDIENTS: BENZALKONIUM CHLORIDE 1.3 mg/1 mL
INACTIVE INGREDIENTS: WATER; DIDECYLDIMONIUM CHLORIDE; METHYLPARABEN; PROPYLPARABEN; PROPYLENE GLYCOL; DIAZOLIDINYL UREA; ALLANTOIN; COCAMIDOPROPYLAMINE OXIDE; CETRIMONIUM CHLORIDE; COCAMIDOPROPYL BETAINE; SODIUM HYDROXIDE

Woodward's HandClens® Foaming Sanitizer & Lotion Color & Fragrance Free

Drug Facts

Active ingredient

Benzalkonium Chloride, 0.13%

Purpose

Antiseptic Hand Sanitizer

Use

for hand sanitizing to decrease bacteria on the skin

Warnings

- For external use only

When using this product

- Avoid contact with eyes. In case of eye contact, flush with water

- Stop use and ask a doctor if rash or irritation develops and lasts

Keep out of reach of children. If swallowed, get medical help or contact a Poison Control Center right away

Directions

- Use enough foam to cover your hands
- Rub hands together briskly until dry

Other information

- Do not store above 110°F (40°C)
- You may report questions or adverse reaction from using this product to 1(541)-476-3178, 8 am to 5 pm (M–F), PST

Inactive ingredients

Water, Cocamidopropylamine Oxide, Didecyldimonium Chloride, Allantoin, Propylene Glycol, Cetrimonium Chloride, Cocamidopropyl Betaine, Sodium Hydroxide, Diazolidinyl Urea, Methylparaben, Propylparaben.

PRINCIPAL DISPLAY PANEL - 50 mL Bottle Label

Fragrance-Free
Color-Free

2 in 1
Sanitizer & Lotion

WOODWARD'S
HandClens®

Foaming Sanitizer & Lotion
Alcohol-Free*• Non-Flammable

Softens Hands with Each Use!

Kills 99.99%
of Germs

1.7 FL OZ (50 mL)